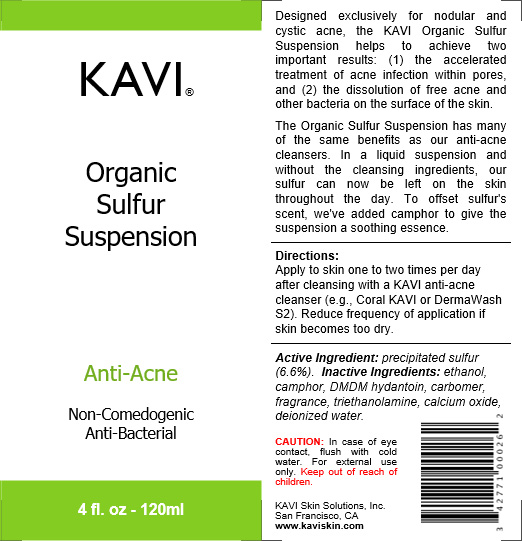 DRUG LABEL: Organic Sulfur Suspension
NDC: 42771-0025 | Form: SUSPENSION
Manufacturer: KAVI Skin Solutions, Inc.
Category: otc | Type: HUMAN OTC DRUG LABEL
Date: 20201020

ACTIVE INGREDIENTS: SULFUR 6.6 g/100 g
INACTIVE INGREDIENTS: TRIETHANOLAMINE BENZOATE 0.035 g/100 g; PHENYLETHYL ALCOHOL 20 g/100 g; LIME (CALCIUM OXIDE) 0.013 g/100 g; DMDM HYDANTOIN 0.2 g/100 g; CARBOMER 1342 0.15 g/100 g; WATER 71.92 g/100 g; CAMPHOR (NATURAL) 10 g/100 g

Organic Sulfur Suspension

Dosage & Administration

Directions:
Apply to skin one to two times per day after cleansing with a KAVI anti-acne cleanser (e.g., Coral KAVI or DermaWash S2). Reduce frequency of application if skin becomes too dry.

Purpose

Designed exclusively for nodular and cystic acne, the KAVI Organic Sulfur Suspension helps to achieve two important results: (1) the accelerated treatment of acne infection within pores, and (2) the dissolution of free acne and other bacteria on the surface of the skin.
The Organic Sulfur Suspension has many of the same benefits as our anti-acne cleansers. In a liquid suspension and without the cleansing ingredients, our sulfur can now be left on the skin throughout the day. To offset sulfur's scent, we've added camphor to give the suspension a soothing essence.

Indications & Usage

The KAVI Organic Sulfur Suspension is best suited for the treatment of acne-prone skin.

Directions:
Apply to skin one to two times per day after cleansing with a KAVI anti-acne cleanser (e.g., Coral KAVI or DermaWash S2). Reduce frequency of application if skin becomes too dry.

Active Ingredients

Active Ingredient: precipitated sulfur (6.6%).

Inactive Ingredients

Inactive Ingredients: ethanol, camphor, DMDM hydantoin, carbomer, fragrance, triethanolamine, calcium oxide, deionized water.

Warnings

For external use only. If swallowed, seek medical attention. Avoid contact with eyes and mucous membranes. In case of eye contact, flush with cold water. Keep out of reach of children.

Keep out of reach of children

CAUTION: For external use only. If swallowed, seek medical attention. Avoid contact with eyes and mucous membranes. In case of eye contact, flush with cold water. Keep out of reach of children.

Back Label - Complete

Designed exclusively for nodular and cystic acne, the KAVI Organic Sulfur Suspension helps to achieve two important results: (1) the accelerated treatment of acne infection within pores, and (2) the dissolution of free acne and other bacteria on the surface of the skin.
The Organic Sulfur Suspension has many of the same benefits as our anti-acne cleansers. In a liquid suspension and without the cleansing ingredients, our sulfur can now be left on the skin throughout the day. To offset sulfur's scent, we've added camphor to give the suspension a soothing essence.

Directions:
Apply to skin one to two times per day after cleansing with a KAVI anti-acne cleanser (e.g., Coral KAVI or DermaWash S2). Reduce frequency of application if skin becomes too dry.

Active Ingredient: precipitated sulfur (6.6%). Inactive Ingredients: ethanol, camphor, DMDM hydantoin, carbomer, fragrance, triethanolamine, calcium oxide, deionized water.

CAUTION: In case of eye contact, flush with cold water. For external use only. Keep out of reach of children.

KAVI Skin Solutions, Inc.
San Francisco, CA www.kaviskin.com

Front and Back Labels

Designed exclusively for nodular and cystic acne, the KAVI Organic Sulfur Suspension helps to achieve two important results: (1) the accelerated treatment of acne infection within pores, and (2) the dissolution of free acne and other bacteria on the surface of the skin.
The Organic Sulfur Suspension has many of the same benefits as our anti-acne cleansers. In a liquid suspension and without the cleansing ingredients, our sulfur can now be left on the skin throughout the day. To offset sulfur's scent, we've added camphor to give the suspension a soothing essence.

Directions:
Apply to skin one to two times per day after cleansing with a KAVI anti-acne cleanser (e.g., Coral KAVI or DermaWash S2). Reduce frequency of application if skin becomes too dry.

Active Ingredient: precipitated sulfur (6.6%). Inactive Ingredients: ethanol, camphor, DMDM hydantoin, carbomer, fragrance, triethanolamine, calcium oxide, deionized water.

CAUTION: In case of eye contact, flush with cold water. For external use only. Keep out of reach of children.

KAVI Skin Solutions, Inc.
San Francisco, CA www.kaviskin.com